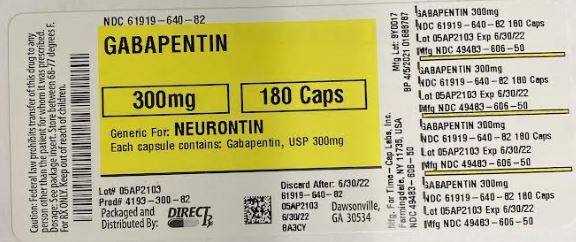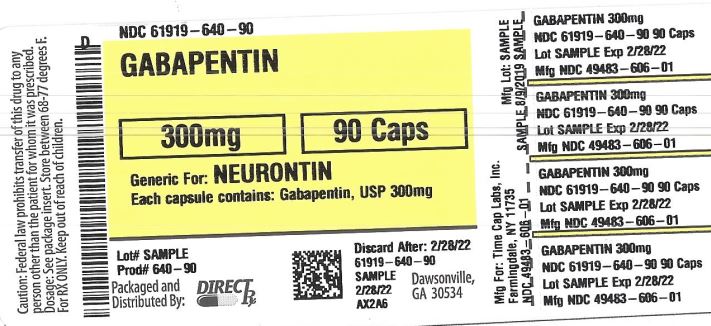 DRUG LABEL: GABAPENTIN
NDC: 61919-640 | Form: CAPSULE
Manufacturer: Direct_Rx
Category: prescription | Type: HUMAN PRESCRIPTION DRUG LABEL
Date: 20230510

ACTIVE INGREDIENTS: GABAPENTIN 300 mg/1 1
INACTIVE INGREDIENTS: FERRIC OXIDE YELLOW; TALC; GELATIN; STARCH, CORN; TITANIUM DIOXIDE; LACTOSE MONOHYDRATE; PROPYLENE GLYCOL; SHELLAC

GABAPENTIN

HOW SUPPLIED

100 mg Capsules (White/White colored, size '3' hard gelatin capsules with "103" printed on body of capsules containing white to off white granular powder) Bottles of 100 & 500
300 mg Capsules (Yellow/Yellow colored, size '1' hard gelatin capsules with "104" printed on body of capsules containing white to off white granular powder) Bottles of 100 & 500
400 mg Capsules (Orange/Orange colored, size '0' hard gelatin capsules with "105" printed on body of capsules containing white to off white granular powder) Bottles of 100 & 500